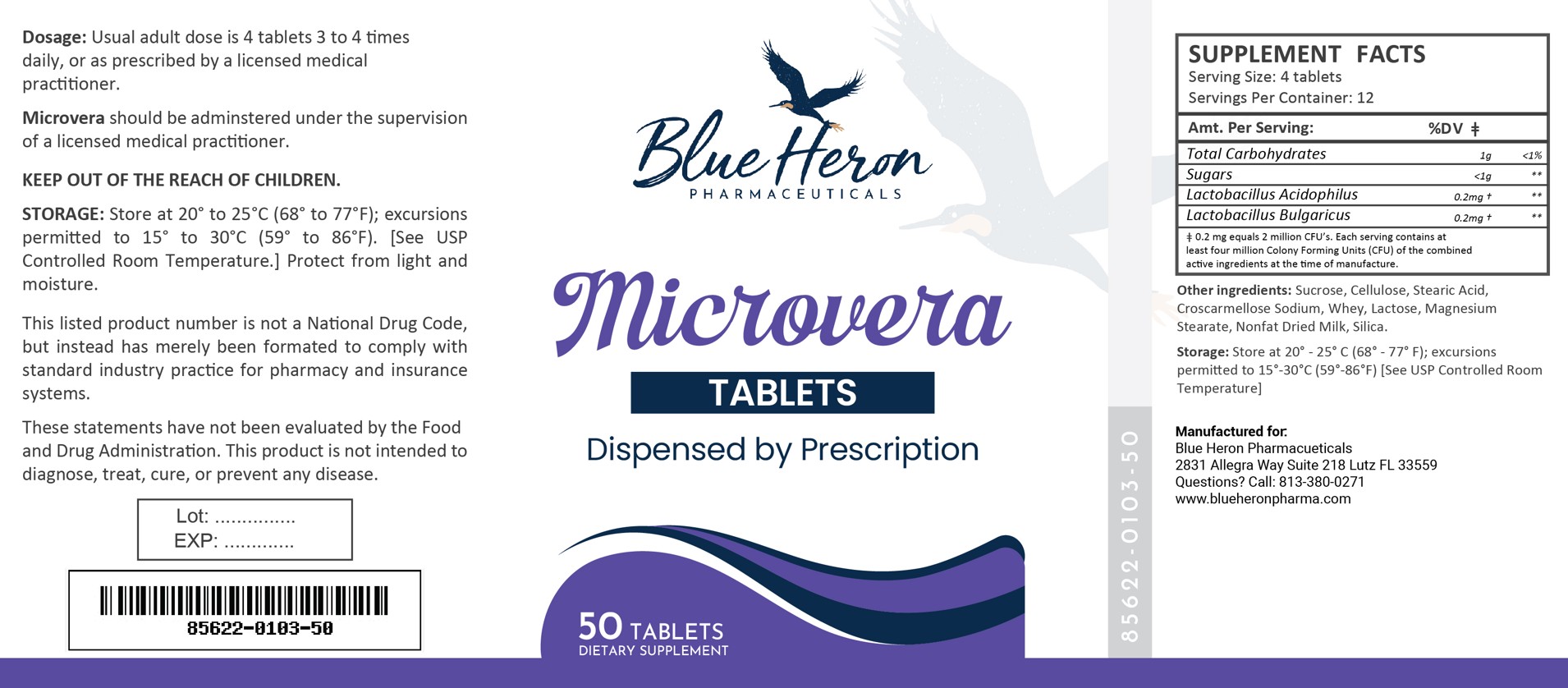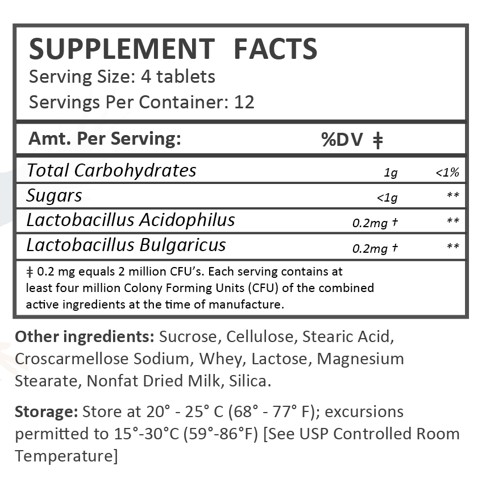 DRUG LABEL: Microvera
NDC: 85622-103 | Form: TABLET
Manufacturer: Blue Heron Pharmaceuticals, LLC
Category: other | Type: DIETARY SUPPLEMENT
Date: 20251009

ACTIVE INGREDIENTS: LACTOBACILLUS ACIDOPHILUS 0.2 mg/1 1; LACTOBACILLUS DELBRUECKII BULGARICUS 0.2 mg/1 1

Microvera

Supplement Facts

Microvera Tablets

Description:

Microvera Probiotic Tablets are white, round tablets dispensed in plastic bottles of 50 ct.

85622-0103-50

Reserved for Professional Recommendation

Microvera Probiotic Tablets should be administered under the supervision of a licensed medical practitioner.

Microvera is an orally administered prescription probiotic formulation for the clinical dietary management of suboptimal nutritional status in patients where advanced supplementation is required and nutritional supplementation in physiologically stressful conditions for maintenance of good health is needed.

This listed product is not a National Drug Code, but instead has merely been formatted to comply with standard industry practice for pharmacy and insurance computer systems.

These statements have not been evaluated by the Food and Drug Administration. This product is not intended to diagnose, treat, cure or prevent any disease.

All prescriptions using this product shall be pursuant to state statutes as applicable. This is not an Orange Book product. This product may be administered only under a physician’s supervision. There are no implied or explicit claims on therapeutic equivalence.

Manufactured for:

Blue Heron Pharmaceuticals

Lutz, FL 33559

Warnings:

This product is contraindicated in patients with a known hypersensitivity to any of the ingredients, including milk products.

Microvera should only be used under the direction and supervision of a licensed medical practitioner. Use with caution in patients that may have a medical condition, are pregnant, lactating, trying to conceive, under the age of 18, or taking medications.

These statements have not been evaluated by the Food and Drug Administration. This product is not intended to diagnose, treat, cure, or prevent any disease.

Dosage:

Usual dosage is 4 tablets 3 to 4 times daily, or as recommended by your healthcare professional.

Packaging:

CONTRAINDICATIONS
This product is contraindicated in patients with known hypersensitivity to any of the ingredients.

PRECAUTIONS
This product is contraindicated in patients with a known hypersensitivity to any of the ingredients.

ADVERSE REACTIONS
Allergic sensitizations have been reported following oral administration of folic acid. Consult your physician immediately if adverse side effects occur.

KEEP OUT OF THE REACH OF CHILDREN.

Storage:

Store at 20° - 25° C (68° - 77° F); excursions permitted to 15°-30°C (59°-86°F) [See USP Controlled Room Temperature]